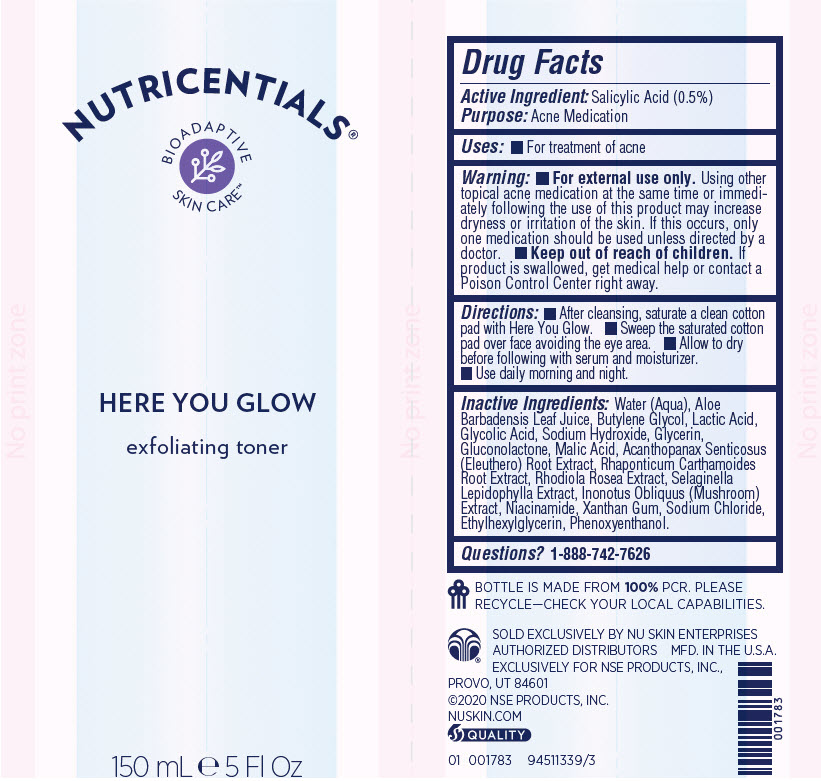 DRUG LABEL: Nutricentials Here You Glow Exfoliating Toner
NDC: 62839-1339 | Form: LIQUID
Manufacturer: NSE Products, Inc.
Category: otc | Type: HUMAN OTC DRUG LABEL
Date: 20250107

ACTIVE INGREDIENTS: Salicylic Acid 5 mg/1 mL
INACTIVE INGREDIENTS: WATER; ALOE VERA LEAF; Butylene Glycol; LACTIC ACID, UNSPECIFIED FORM; Glycolic Acid; Sodium Hydroxide; Glycerin; Malic Acid; Gluconolactone; PHENOXYETHANOL; Sodium Chloride; Niacinamide; Xanthan Gum; Ethylhexylglycerin; SEDUM ROSEUM ROOT; INONOTUS OBLIQUUS FRUITING BODY; ELEUTHERO; LEUZEA CARTHAMOIDES ROOT

Nutricentials® Here You Glow Exfoliating Toner

Drug Facts

Active Ingredient

Salicylic Acid (0.5%)

Purpose

Acne Medication

Uses

- For treatment of acne

Warning

- For external use only. Using other topical acne medication at the same time or immediately following the use of this product may increase dryness or irritation of the skin. If this occurs, only one medication should be used unless directed by a doctor.

- Keep out of reach of children. If product is swallowed, get medical help or contact a Poison Control Center right away.

Directions

- After cleansing, saturate a clean cotton pad with Here You Glow.
- Sweep the saturated cotton pad over face avoiding the eye area.
- Allow to dry before following with serum and moisturizer.
- Use daily morning and night.

Inactive Ingredients

Water (Aqua), Aloe Barbadensis Leaf Juice, Butylene Glycol, Lactic Acid, Glycolic Acid, Sodium Hydroxide, Glycerin, Gluconolactone, Malic Acid, Acanthopanax Senticosus (Eleuthero) Root Extract, Rhaponticum Carthamoides Root Extract, Rhodiola Rosea Extract, Selaginella Lepidophylla Extract, Inonotus Obliquus (Mushroom) Extract, Niacinamide, Xanthan Gum, Sodium Chloride, Ethylhexylglycerin, Phenoxyenthanol.

Questions?

1-888-742-7626

PRINCIPAL DISPLAY PANEL - 150 mL Bottle Label

NUTRICENTIALS®

BIOADAPTIVE
SKIN CARE™

HERE YOU GLOW
exfoliating toner

150 mL ℮ 5 Fl Oz